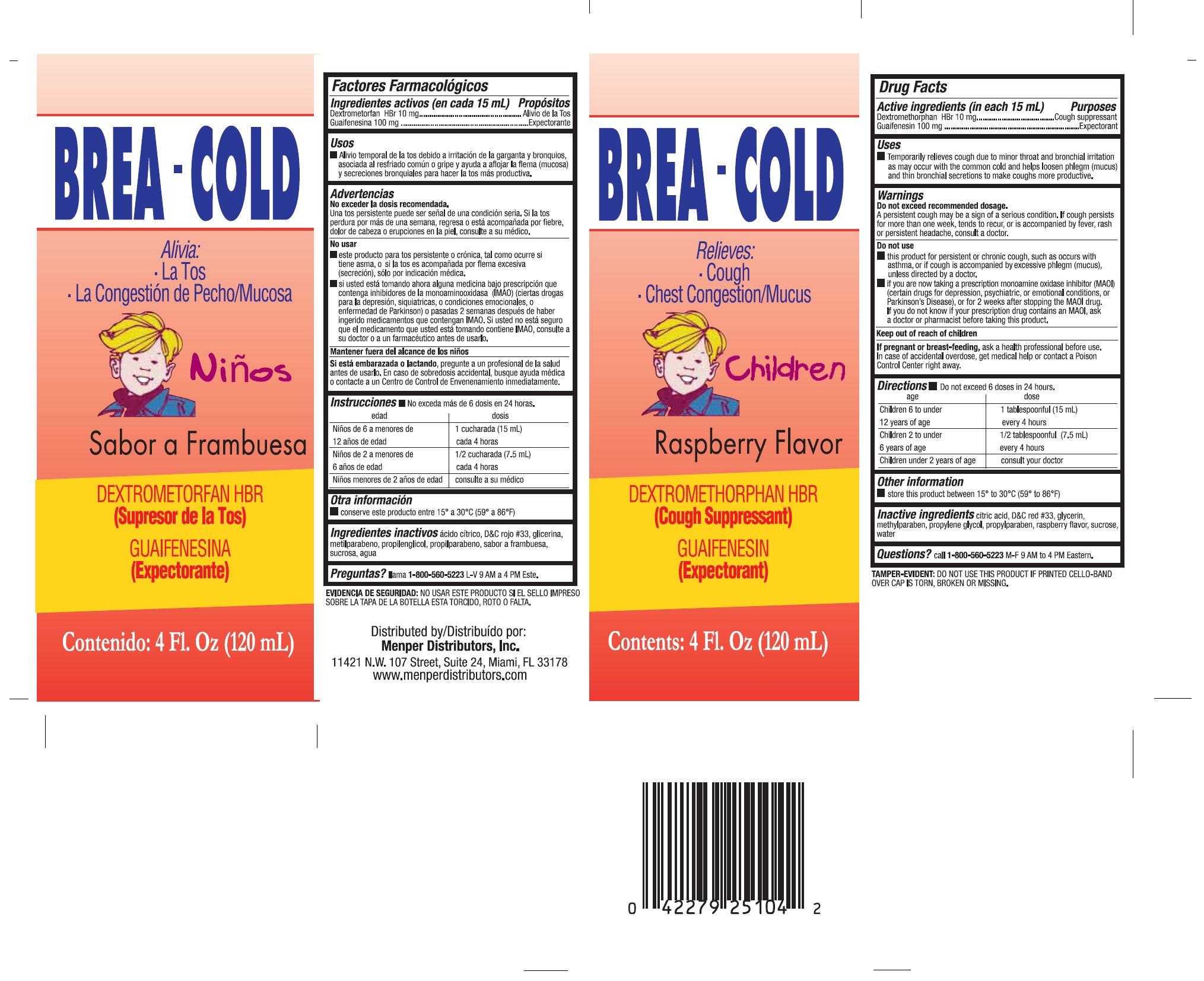 DRUG LABEL: Breacold Children
NDC: 53145-007 | Form: LIQUID
Manufacturer: Menper Distributors, Inc.
Category: otc | Type: HUMAN OTC DRUG LABEL
Date: 20220218

ACTIVE INGREDIENTS: GUAIFENESIN 100 mg/15 mL; DEXTROMETHORPHAN HYDROBROMIDE 10 mg/15 mL
INACTIVE INGREDIENTS: CITRIC ACID ACETATE; D&C RED NO. 33; GLYCERIN; METHYLPARABEN; RASPBERRY; PROPYLENE GLYCOL; PROPYLPARABEN; WATER; SUCROSE

Active ingredients (in each 15mL tsp)

Guaifenesin 100 mg………………………………Expectorant

Dextromethorphan HBr 10 mg……………………Cough suppressant

purpose

Expectorant

Cough Suppressant

Uses

Temporarily relieves cough due to minor throat and bronchial irritation as may occur with the commun cold and help loosen phleg, (mucus) and thin bronchial secretions to make coughs more productive.

Warnings Do not exceed recommended dosage.

- A persistent cough may be a sign of a serious condition. If cough persists for more than one week, tends to recur, or is accompanied by fever, rash, or persistent headache, consult a doctor.

Do not use:

- This product for persistent or chronic cough, such as occurs with asthma, or if cough is accompanied by excessive phlegm (mucus), unless directed by a doctor.
- if you are now taking a prescription monoamine oxidase inhibitor (MAOI) (certain drugs for depression, psychiatric or emotional conditions, or Parkinson’s disease), or for 2 weeks after stopping the MAOI drug. If you do not know if your prescription drug contains an MAOI, ask a doctor or pharmacist before taking this product.

Keep out of reach of children.

If you are pregnant or breast-feeding,

ask a health professional before use. In case of accidental overdose, get medical help or contact a Poison Control Center right away.

Directions

Do not exceed 6 doses in 24 hours.

Age Dose

Children 6 to under 1 teaspoonful (5 mL)

12 years of age..................................................... every 4 hours

Children 2 to under 1/2 teaspoonful (2.5 mL)

6 years of age....................................................... every 4 hours

Children under 2 years of age.................................. consult your doctor

Other information

Store this product between 15°-30°C (59°-86°F)

Inactive ingredients

Citric acid, D&C red #33, glycerin, methylparaben, propylene glycol, propylparaben , raspberry flavor, sucrose, water

Questions?

Call 1-800-560-5223 M-F 9 AM to 4 PM Eastern.